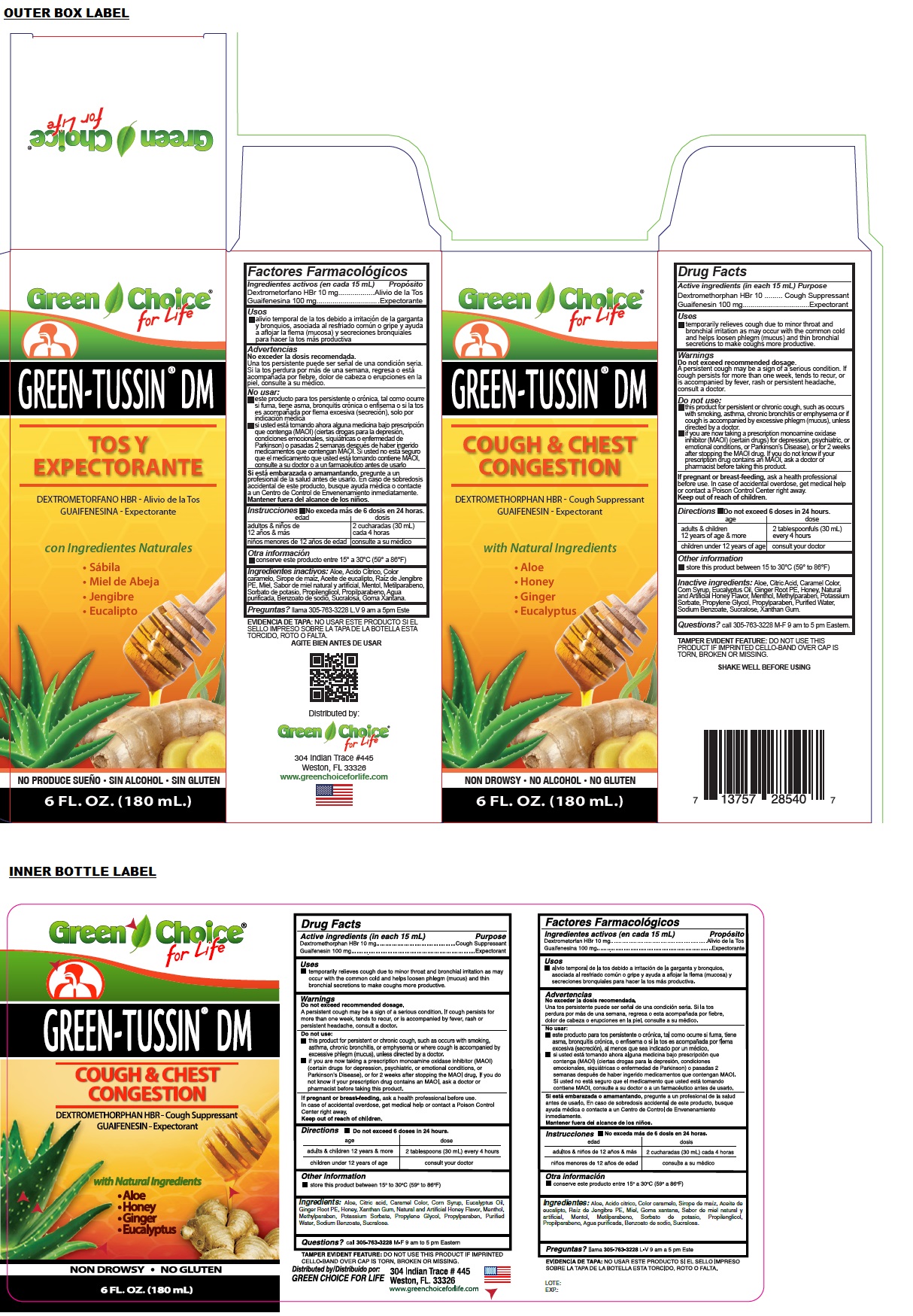 DRUG LABEL: GREEN TUSSIN DM
NDC: 55287-540 | Form: LIQUID
Manufacturer: Green Choice for Life
Category: otc | Type: HUMAN OTC DRUG LABEL
Date: 20240314

ACTIVE INGREDIENTS: DEXTROMETHORPHAN HYDROBROMIDE 10 mg/15 mL; GUAIFENESIN 100 mg/15 mL
INACTIVE INGREDIENTS: ALOE; CITRIC ACID MONOHYDRATE; CARAMEL; CORN SYRUP; EUCALYPTUS OIL; GINGER; HONEY; MENTHOL, UNSPECIFIED FORM; METHYLPARABEN; POTASSIUM SORBATE; PROPYLENE GLYCOL; PROPYLPARABEN; WATER; SODIUM BENZOATE; SUCRALOSE; XANTHAN GUM

GREEN-TUSSIN® DM

Active ingredients (in each 15 mL)

Dextromethorphan HBr 10 mg
Guaifenesin 100 mg

Purpose

Cough Suppressant
Expectorant

Uses

• temporarily relieves cough due to minor throat and bronchial irritation as may occur with the common cold and helps loosen phlegm (mucus) and thin bronchial secretions to make coughs more productive.

Warnings

Do not exceed recommended dosage.
A persistent cough may be a sign of a serious condition. If cough persists for more than one week, tends to recur, or is accompanied by fever, rash or persistent headache, consult a doctor.

Do not use:
• this product for persistent or chronic cough, such as occurs with smoking, asthma, chronic bronchitis or emphysema or if cough is accompanied by excessive phlegm (mucus), unless directed by a doctor.
• if you are now taking a prescription monoamine oxidase inhibitor (MAOI) (certain drugs) for depression, psychiatric, or emotional conditions, or Parkinson's Disease), or for 2 weeks after stopping the MAOI drug. If you do not know if your prescription drug contains an MAOI, ask a doctor or pharmacist before taking this product.

If pregnant or breast-feeding, ask a health professional before use. In case of accidental overdose, get medical help or contact a Poison Control Center right away.

Keep out of reach of children.

Directions

• Do not exceed 6 doses in 24 hours.

age | dose
adults & children 12 years of age & more | 2 tablespoonfuls (30 mL) every 4 hours
children under 12 years of age | consult your doctor

Other information

• store this product between 15 to 30°C (59° to 86°F)

Inactive ingredients:

Aloe, Citric Acid, Caramel Color, Corn Syrup, Eucalyptus Oil, Ginger Root PE, Honey, Natural and Artificial Honey Flavor, Menthol, Methylparaben, Potassium Sorbate, Propylene Glycol, Propylparaben, Purified Water, Sodium Benzoate, Sucralose, Xanthan Gum.

Questions?

call 305-763-3228 M-F 9 am to 5 pm Eastern.

COUGH & CHEST CONGESTION

with Natural Ingredients

• Aloe
• Honey
• Ginger
• Eucalyptus

NON DROWSY • NO ALCOHOL • NO GLUTEN

TAMPER EVIDENT FEATURE: DO NOT USE THIS PRODUCT IF IMPRINTED CELLO-BAND OVER CAP IS TORN, BROKEN OR MISSING.

SHAKE WELL BEFORE USING

Distributed by:
Green Choice for Life
304 Indian Trace #445
Weston, FL 33326

www.greenchoiceforlife.com